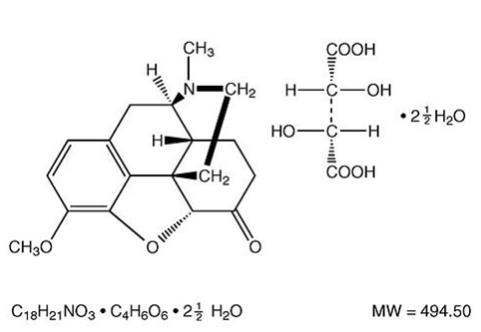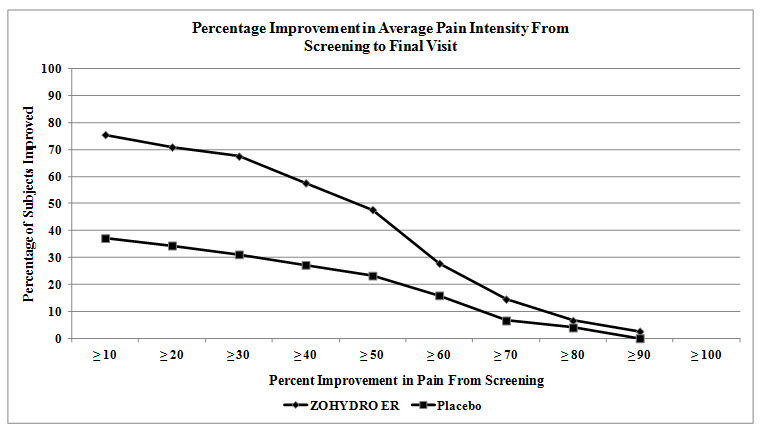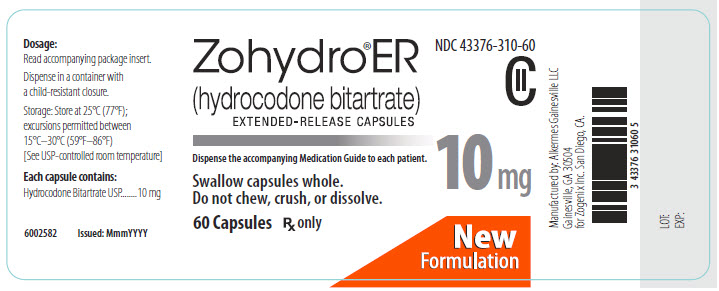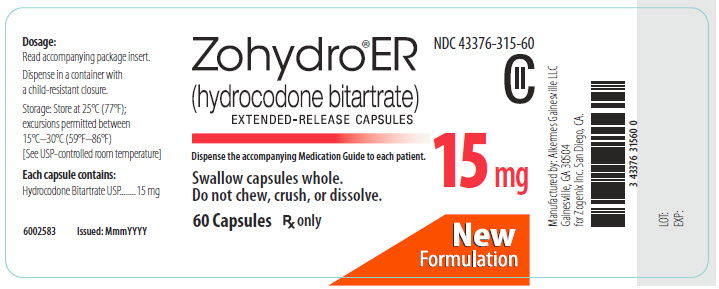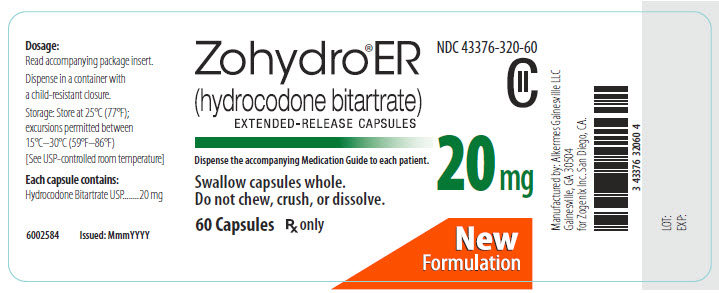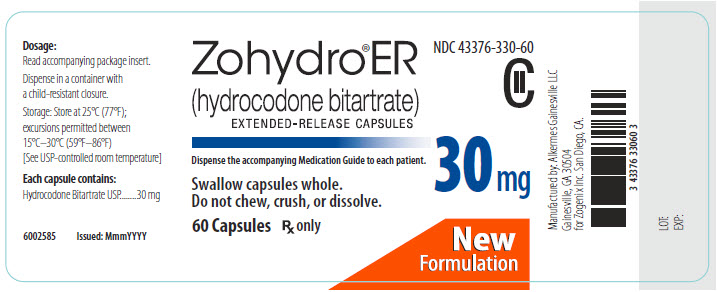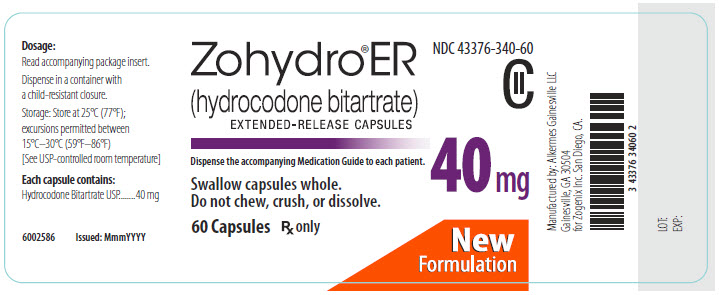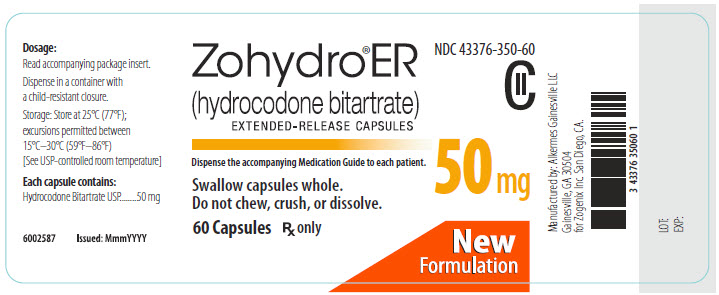 DRUG LABEL: Zohydro
NDC: 43376-310 | Form: CAPSULE, EXTENDED RELEASE
Manufacturer: Zogenix, Inc.
Category: prescription | Type: HUMAN PRESCRIPTION DRUG LABEL
Date: 20150225
DEA Schedule: CII

ACTIVE INGREDIENTS: HYDROCODONE BITARTRATE 10 mg/1 1
INACTIVE INGREDIENTS: SUCROSE; HYPROMELLOSES; AMMONIO METHACRYLATE COPOLYMER TYPE B; SILICON DIOXIDE; TALC; POLYETHYLENE GLYCOLS; POVIDONES; TITANIUM DIOXIDE; FD&C BLUE NO. 1; FD&C RED NO. 40; FERRIC OXIDE YELLOW; FD&C RED NO. 3; FERROSOFERRIC OXIDE; FERRIC OXIDE RED; GELATIN

HIGHLIGHTS OF PRESCRIBING INFORMATION

These highlights do not include all the information needed to use ZOHYDRO® ER safely and effectively. See full prescribing information for ZOHYDRO® ER.
ZOHYDRO® ER (hydrocodone bitartrate) extended‑release capsules, for
oral use, CII
Initial U.S. Approval: 1943

WARNING: ADDICTION, ABUSE, AND MISUSE; LIFE-THREATENING RESPIRATORY DEPRESSION; ACCIDENTAL INGESTION; NEONATAL OPIOID WITHDRAWAL SYNDROME; INTERACTION WITH ALCOHOL; and CYTOCHROME P450 3A4 INTERACTION

See full prescribing information for complete boxed warning.

- ZOHYDRO ER exposes users to risks of addiction, abuse, and misuse, which can lead to overdose and death. Assess each patient’s risk before prescribing, and monitor regularly for development of these behaviors or conditions. (5.1)
- Serious, life-threatening, or fatal respiratory depression may occur. Monitor closely, especially upon initiation or following a dose increase. Instruct patients to swallow ZOHYDRO ER whole to avoid exposure to a potentially fatal dose of hydrocodone. (5.2)
- Accidental ingestion of ZOHYDRO ER, especially in children, can result in a fatal overdose of hydrocodone. (5.2)
- Prolonged use of ZOHYDRO ER during pregnancy can result in neonatal opioid withdrawal syndrome, which may be life-threatening if not recognized and treated. If opioid use is required for a prolonged period in a pregnant woman, advise the patient of the risk of neonatal opioid withdrawal syndrome and ensure that appropriate treatment will be available. (5.3)
- Instruct patients not to consume alcohol or any products containing alcohol while taking ZOHYDRO ER because co-ingestion can result in fatal plasma hydrocodone levels. (5.4)
- Initiation of CYP3A4 inhibitors (or discontinuation of CYP3A4 inducers) can result in a fatal overdose of hydrocodone from ZOHYDRO ER. (5.13)

RECENT MAJOR CHANGES

Boxed Warning 8/2014
Dosage and Administration (2) 1/2015
Warnings and Precautions (5) 8/2014

1 INDICATIONS AND USAGE

ZOHYDRO ER is an opioid agonist indicated for the management of pain severe enough to require daily, around-the-clock, long-term opioid treatment and for which alternative treatment options are inadequate. (1)

Limitations of Use

- Because of the risks of addiction, abuse, and misuse with opioids, even at recommended doses, and because of the greater risks of overdose and death with extended-release opioid formulations, reserve ZOHYDRO ER for use in patients for whom alternative treatment options (e.g., non-opioid analgesics or immediate-release opioids) are ineffective, not tolerated, or would be otherwise inadequate to provide sufficient management of pain. (1)
- ZOHYDRO ER is not indicated as an as-needed (prn) analgesic. (1)

2 DOSAGE AND ADMINISTRATION

- ZOHYDRO ER 50 mg capsules, a single dose greater than 40 mg, or a total daily dose greater than 80 mg are only for use in patients in whom tolerance to an opioid of comparable potency has been established. (2.1)
- For opioid-naïve and opioid non-tolerant patients, initiate with 10 mg capsules orally every 12 hours. (2.1)
- To convert to ZOHYDRO ER from another opioid, use available conversion factors to obtain estimated dose. (2.1)
- Dose can be increased every 3 to 7 days, using increments of 10 mg every 12 hours (i.e., 20 mg per day). (2.1, 2.2)
- Do not abruptly discontinue ZOHYDRO ER in a physically dependent patient. (2.3)
- Capsules must be swallowed intact and are not to be cut, broken, chewed, crushed, or dissolved (risk of fatal overdose). (2.1, 5.1)

3 DOSAGE FORMS AND STRENGTHS

Extended-release capsules: 10 mg, 15 mg, 20 mg, 30 mg, 40 mg, and 50 mg (3)

4 CONTRAINDICATIONS

- Significant respiratory depression (4)
- Acute or severe bronchial asthma (4)
- Known or suspected paralytic ileus (4)
- Hypersensitivity to hydrocodone bitartrate (4)

5 WARNINGS AND PRECAUTIONS

See Boxed WARNINGS

- Interactions with CNS depressants: Concomitant use may cause profound sedation, respiratory depression, and death. If coadministration is required, consider dose reduction of one or both drugs. (5.4)
- Elderly, cachectic, debilitated patients, and those with chronic pulmonary disease: Monitor closely because of increased risk for life-threatening respiratory depression. (5.5, 5.6)
- Hypotensive effects: Monitor during dose initiation and titration. (5.7)
- Patients with head injury or increased intracranial pressure: Monitor for sedation and respiratory depression. Avoid use of ZOHYDRO ER in patients with impaired consciousness or coma susceptible to intracranial effects of CO2 retention. (5.8)
- Concomitant use of CYP3A4 inhibitors may increase opioid effects. (5.13)

6 ADVERSE REACTIONS

Adverse reactions in ≥2% of patients in placebo-controlled trials include constipation, nausea, somnolence, fatigue, headache, dizziness, dry mouth, vomiting, pruritus, abdominal pain, edema peripheral, upper respiratory tract infection, muscle spasms, urinary tract infection, back pain, and tremor. (6.1)

To report SUSPECTED ADVERSE REACTIONS, contact Zogenix, Inc. at 1-866-ZOGENIX or FDA at 1-800-FDA-1088 or www.fda.gov/medwatch.

7 DRUG INTERACTIONS

- Mixed agonists/antagonists and partial agonist analgesics: Avoid use with ZOHYDRO ER because they may reduce analgesic effect of ZOHYDRO ER or precipitate withdrawal symptoms. (7.4)
- The use of MAO inhibitors or tricyclic antidepressants with ZOHYDRO ER may increase the effect of either the antidepressant or ZOHYDRO ER. (7.5)

8 USE IN SPECIFIC POPULATIONS

- Pregnancy: May cause fetal harm. (8.1)
- Lactation: Not recommended. (8.2)
- Hepatic impairment: No adjustment in starting dose with ZOHYDRO ER is required in patients with mild or moderate hepatic impairment; however, in patients with severe hepatic impairment, start with the lowest dose, 10 mg. Monitor these patients closely for adverse events such as respiratory depression. (8.6)
- Renal impairment: Use a low initial dose of ZOHYDRO ER in patients with renal impairment and monitor closely for adverse events such as respiratory depression. (8.7)

FULL PRESCRIBING INFORMATION

WARNING: ADDICTION, ABUSE, AND MISUSE; LIFE-THREATENING RESPIRATORY DEPRESSION; ACCIDENTAL INGESTION; NEONATAL OPIOID WITHDRAWAL SYNDROME; INTERACTION WITH ALCOHOL; and CYTOCHROME P450 3A4 INTERACTION

Addiction, Abuse, and Misuse
ZOHYDRO ER exposes patients and other users to the risks of opioid addiction, abuse, and misuse, which can lead to overdose and death. Assess each patient’s risk prior to prescribing ZOHYDRO ER and monitor all patients regularly for the development of these behaviors or conditions [see Warnings and Precautions (5.1)].

Life-threatening Respiratory Depression
Serious, life-threatening, or fatal respiratory depression may occur with use of ZOHYDRO ER. Monitor for respiratory depression, especially during initiation of ZOHYDRO ER or following a dose increase. Instruct patients to swallow ZOHYDRO ER capsules whole; crushing, chewing, or dissolving ZOHYDRO ER capsules can cause rapid release and absorption of a potentially fatal dose of hydrocodone [see Warnings and Precautions (5.2)].

Accidental Ingestion
Accidental ingestion of even one dose of ZOHYDRO ER, especially by children, can result in a fatal overdose of hydrocodone [see Warnings and Precautions (5.2)].

Neonatal Opioid Withdrawal Syndrome
Prolonged use of ZOHYDRO ER during pregnancy can result in neonatal opioid withdrawal syndrome, which may be life-threatening if not recognized and treated, and requires management according to protocols developed by neonatology experts. If opioid use is required for a prolonged period in a pregnant woman, advise the patient of the risk of neonatal opioid withdrawal syndrome and ensure that appropriate treatment will be available [see Warnings and Precautions (5.3)].

Interaction with Alcohol
Instruct patients not to consume alcoholic beverages or use prescription or non-prescription products that contain alcohol while taking ZOHYDRO ER. The co-ingestion of alcohol with ZOHYDRO ER may result in increased plasma levels and a potentially fatal overdose of hydrocodone [see Warnings and Precautions (5.4) and Clinical Pharmacology (12.3)].

Cytochrome P450 3A4 Interaction
The concomitant use of ZOHYDRO ER with all cytochrome P450 3A4 inhibitors may result in an increase in hydrocodone plasma concentrations, which could increase or prolong adverse drug effects and may cause potentially fatal respiratory depression. In addition, discontinuation of a concomitantly used cytochrome P450 3A4 inducer may result in an increase in hydrocodone plasma concentration. Monitor patients receiving ZOHYDRO ER and any CYP3A4 inhibitor or inducer [see Warnings and Precautions (5.13) and Clinical Pharmacology (12.3)].

1 INDICATIONS AND USAGE

ZOHYDRO® ER (hydrocodone bitartrate) is indicated for the management of pain severe enough to require daily, around-the-clock, long-term opioid treatment and for which alternative treatment options are inadequate.

Limitations of Use

- Because of the risks of addiction, abuse, and misuse with opioids, even at recommended doses, and because of the greater risks of overdose and death with extended-release opioid formulations, reserve ZOHYDRO ER for use in patients for whom alternative treatment options (e.g., non-opioid analgesics or immediate-release opioids) are ineffective, not tolerated, or would be otherwise inadequate to provide sufficient management of pain.
- ZOHYDRO ER is not indicated as an as-needed (prn) analgesic.

2 DOSAGE AND ADMINISTRATION

2.1 Initial Dosing

ZOHYDRO ER should be prescribed only by healthcare professionals who are knowledgeable in the use of potent opioids for the management of chronic pain.

ZOHYDRO ER 50 mg capsules, a single dose of ZOHYDRO ER greater than 40 mg, or a total daily dose greater than 80 mg are only for use in patients in whom tolerance to an opioid of comparable potency has been established. Patients who are opioid tolerant are those receiving, for one week or longer, at least 60 mg oral morphine per day, 25 mcg transdermal fentanyl per hour, 30 mg oral oxycodone per day, 8 mg oral hydromorphone per day, 25 mg oral oxymorphone per day, or an equianalgesic dose of another opioid.

Initiate the dosing regimen for each patient individually, taking into account the patient's prior analgesic treatment experience and risk factors for addiction, abuse, and misuse [see Warnings and Precautions (5.1)]. Monitor patients closely for respiratory depression, especially within the first 24-72 hours of initiating therapy with ZOHYDRO ER [see Warnings and Precautions (5.2)].

ZOHYDRO ER must be taken whole [see Patient Counseling Information (17)]. Crushing, chewing, or dissolving the beads in ZOHYDRO ER capsules will result in uncontrolled delivery of hydrocodone and can lead to overdose or death [see Warnings and Precautions (5.1)].

Use of ZOHYDRO ER as the First Opioid Analgesic
Initiate treatment with ZOHYDRO ER with one 10 mg capsule every 12 hours.

Use of ZOHYDRO ER in Patients Who Are Not Opioid Tolerant
The starting dose for patients who are not opioid tolerant is ZOHYDRO ER 10 mg orally every 12 hours. Patients who are opioid tolerant are those receiving, for one week or longer, at least 60 mg oral morphine per day, 25 mcg transdermal fentanyl per hour, 30 mg oral oxycodone per day, 8 mg oral hydromorphone per day, 25 mg oral oxymorphone per day, or an equianalgesic dose of another opioid.

Use of higher starting doses in patients who are not opioid tolerant may cause fatal respiratory depression.

Conversion from Other Oral Opioids to ZOHYDRO ER
Discontinue all other around-the-clock opioid drugs when ZOHYDRO ER therapy is initiated.

While there are useful tables of opioid equivalents readily available, there is substantial inter-patient variability in the relative potency of different opioid drugs and products. As such, it is preferable to underestimate a patient’s 24-hour oral hydrocodone requirements and provide rescue medication (e.g., immediate-release opioid) than to overestimate the 24-hour oral hydrocodone requirements which could result in adverse reactions. In a ZOHYDRO ER clinical trial with an open label titration period, patients were converted from their prior opioid to ZOHYDRO ER using Table 1 as a guide for the initial ZOHYDRO ER dose.

Consider the following when using the information in Table 1:

- This is not a table of equianalgesic doses.
- The conversion factors in this table are only for the conversion from one of the listed oral opioid analgesics to ZOHYDRO ER.
- The table cannot be used to convert from ZOHYDRO ER to another opioid. Doing so will result in an over-estimation of the dose of the new opioid and may result in fatal overdose.

Table 1.
Conversion Factors to ZOHYDRO ER (Not Equianalgesic Doses)
Prior Oral Opioid | Oral Dose (mg) | Approximate Oral Conversion Factor
Hydrocodone | 10 | 1
Oxycodone | 10 | 1
Methadone | 10 | 1
Oxymorphone | 5 | 2
Hydromorphone | 3.75 | 2.67
Morphine | 15 | 0.67
Codeine | 100 | 0.10
The conversion ratios in this table are only to be used for the conversion from current opioid therapy to ZOHYDRO ER.

To calculate the estimated daily ZOHYDRO ER dose using Table 1:

- For patients on a single opioid, sum the current total daily dose of the opioid and then multiply the total daily dose by the conversion factor to calculate the approximate oral hydrocodone daily dose. The daily dose should then be divided in half for administration every 12 hours.
- For patients on a regimen of more than one opioid, calculate the approximate oral hydrocodone dose for each opioid and sum the totals to obtain approximate total hydrocodone daily dose. The daily dose should then be divided in half for administration every 12 hours.
- For patients on a regimen of fixed-ratio opioid/non-opioid analgesic products, use only the opioid component of these products in the conversion.

Always round the dose down, if necessary, to the appropriate ZOHYDRO ER strength(s) available.

Example conversion from a single opioid to ZOHYDRO ER

Step 1: Sum the total daily dose of the opioid (in this case, extended-release oxymorphone); 15 mg oxymorphone twice daily = 30 mg total daily dose of oxymorphone.

Step 2: Calculate the approximate equivalent dose of oral hydrocodone based on the total daily dose of the current opioid using Table 1; 30 mg total daily dose of oxymorphone x 2 = 60 mg of oral hydrocodone daily. The daily dose should then be divided in half for administration every 12 hours.

Step 3: Calculate the approximate starting dose which is 30 mg ZOHYDRO ER every 12 hours. Round down, if necessary, to the appropriate ZOHYDRO ER capsule strengths available. Close observation and frequent titration are warranted until pain management is stable on the new opioid. Monitor patients for signs and symptoms of opioid withdrawal or for signs of over-sedation/toxicity after converting patients to ZOHYDRO ER.

The dose of ZOHYDRO ER can be gradually adjusted preferably at increments of 10 mg every 12 hours every 3 to 7 days, until adequate pain relief and acceptable adverse reactions have been achieved.

Conversion from Methadone to ZOHYDRO ER
Close monitoring is of particular importance when converting from methadone to other opioid agonists. The ratio between methadone and other opioid agonists may vary widely as a function of previous dose exposure. Methadone has a long half-life and tends to accumulate in the plasma.

Conversion from Transdermal Fentanyl to ZOHYDRO ER
ZOHYDRO ER treatment can be initiated 18 hours following the removal of the transdermal fentanyl patch. Although there has been no systematic assessment of such conversion, a conservative hydrocodone dose, approximately 10 mg every 12 hours of ZOHYDRO ER, should be initially substituted for each 25 mcg/hr fentanyl transdermal patch. Follow the patient closely during conversion from transdermal fentanyl to ZOHYDRO ER, as there is limited documented experience with this conversion.

2.2 Titration and Maintenance of Therapy

Individually titrate ZOHYDRO ER to a dose that provides adequate analgesia and minimizes adverse reactions. Continually reevaluate patients receiving ZOHYDRO ER to assess the maintenance of pain control and the relative incidence of adverse reactions, as well as monitoring for the development of addiction, abuse, or misuse. Frequent communication is important among the prescriber, other members of the healthcare team, the patient, and the caregiver/family during periods of changing analgesic requirements, including initial titration. During chronic therapy, periodically reassess the continued need for opioid analgesics. Patients who experience breakthrough pain may require a dose increase of ZOHYDRO ER, or may need a rescue medication with an appropriate dose of an immediate-release analgesic. If the level of pain increases after dose stabilization, attempt to identify the source of increased pain while adjusting the ZOHYDRO ER dose to decrease the level of pain. Because steady-state plasma concentrations are approximated within 3 days, ZOHYDRO ER dosage adjustments, preferably at increments of 10 mg every 12 hours, may be done every 3 to 7 days. If unacceptable opioid-related adverse reactions are observed, the subsequent doses may be reduced. Adjust the dose to obtain an appropriate balance between management of pain and opioid-related adverse reactions.

2.3 Discontinuation of ZOHYDRO ER

When a patient no longer requires therapy with ZOHYDRO ER, use a gradual downward titration of the dose every 2 to 4 days to prevent signs and symptoms of withdrawal in the physically-dependent patient. During the Phase 3 study, the following taper schedule was utilized for patients assigned to placebo in the treatment phase of the study (Table 2):

Table 2.
ZOHYDRO ER Taper Schedule Used in Phase 3 Study
Stabilized Dose At Time of Taper Initiation | Taper Schedule
20 mg to 30 mg q12h* | - 10 mg q12h on Days 1 and 2 - Day 3, stop
40 mg to 70 mg q12h | - 40 mg q12h on Days 1 and 2 - 20 mg q12h on Days 3 and 4 - 10 mg q12h on Days 5 and 6 - Day 7, stop
80 mg to 100 mg q12h | - 80 mg q12h on Days 1 and 2 - 60 mg q12h on Days 3 and 4 - 40 mg q12h on Days 5 and 6 - 20 mg q12h on Days 7 and 8 - 10 mg q12h on Days 9 and 10 - Day 11, stop

*q12h = every 12 hours

Doses above 100 mg every 12 hours (q12h) were not studied in the Phase 3 trial. For patients exceeding 100 mg q12h use a gradual downward titration of the dose every 2 to 4 days. Patients should be monitored closely for signs and symptoms of opioid withdrawal which may indicate a need to taper more slowly. Do not abruptly discontinue ZOHYDRO ER.

2.4 Administration of ZOHYDRO ER

Instruct patients to swallow ZOHYDRO ER capsules whole. The beads in the capsules are not to be crushed, dissolved, or chewed due to the risk of rapid release and absorption of a potentially fatal dose of hydrocodone [see Warnings and Precautions (5.1)].

2.5 Hepatic Impairment

Patients with hepatic impairment may have higher plasma concentrations of hydrocodone than those with normal function. No adjustment in starting dose with ZOHYDRO ER is required in patients with mild or moderate hepatic impairment. However, in patients with severe hepatic impairment, start with the lowest dose, 10 mg every 12 hours. Monitor these patients closely for adverse events such as respiratory depression [see Clinical Pharmacology (12.3)].

2.6 Renal Impairment

Patients with renal impairment may have higher plasma concentrations of hydrocodone than those with normal function. Initiate therapy with a low initial dose of ZOHYDRO ER in patients with renal impairment and monitor closely for respiratory depression and sedation [see Clinical Pharmacology (12.3)].

3 DOSAGE FORMS AND STRENGTHS

ZOHYDRO ER (hydrocodone) extended-release capsules are available in 10 mg, 15 mg, 20 mg, 30 mg, 40 mg, and 50 mg hard gelatin capsules for oral administration, containing white to off-white beads, roughly spherical in shape, and uniform in appearance.

4 CONTRAINDICATIONS

ZOHYDRO ER is contraindicated in patients with:

- Significant respiratory depression
- Acute or severe bronchial asthma in an unmonitored setting or in the absence of resuscitative equipment
- Known or suspected paralytic ileus
- Hypersensitivity (e.g., anaphylaxis) to hydrocodone bitartrate or any other ingredients in ZOHYDRO ER

5 WARNINGS AND PRECAUTIONS

5.1 Addiction, Abuse, and Misuse

ZOHYDRO ER contains hydrocodone, a Schedule II controlled substance. As an opioid, ZOHYDRO ER exposes users to the risks of addiction, abuse, and misuse [see Drug Abuse and Dependence (9)]. As modified-release products such as ZOHYDRO ER deliver the opioid over an extended period of time, there is a greater risk for overdose and death due to the larger amount of hydrocodone present.

Although the risk of addiction in any individual is unknown, it can occur in patients appropriately prescribed ZOHYDRO ER and in those who obtain the drug illicitly. Addiction can occur at recommended doses and if the drug is misused or abused.

Assess each patient’s risk for opioid addiction, abuse, or misuse prior to prescribing ZOHYDRO ER, and monitor all patients receiving ZOHYDRO ER for the development of these behaviors or conditions. Risks are increased in patients with a personal or family history of substance abuse (including drug or alcohol addiction or abuse) or mental illness (e.g., major depression). The potential for these risks should not, however, prevent the prescribing of ZOHYDRO ER for the proper management of pain in any given patient. Patients at increased risk may be prescribed modified-release opioid formulations such as ZOHYDRO ER, but use in such patients necessitates intensive counseling about the risks and proper use of ZOHYDRO ER along with intensive monitoring for signs of addiction, abuse, and misuse.

Abuse or misuse of ZOHYDRO ER by crushing, chewing, snorting, or injecting the dissolved product will result in the uncontrolled delivery of the hydrocodone and can result in overdose and death [see Overdosage (10)].

Opioid agonists such as ZOHYDRO ER are sought by drug abusers and people with addiction disorders and are subject to criminal diversion. Consider these risks when prescribing or dispensing ZOHYDRO ER. Strategies to reduce these risks include prescribing the drug in the smallest appropriate quantity and advising the patient on the proper disposal of unused drug [see Patient Counseling Information (17)]. Contact local state professional licensing board or state controlled substances authority for information on how to prevent and detect abuse or diversion of this product.

5.2 Life-Threatening Respiratory Depression

Serious, life-threatening, or fatal respiratory depression has been reported with the use of modified-release opioids, even when used as recommended. Respiratory depression from opioid use, if not immediately recognized and treated, may lead to respiratory arrest and death. Management of respiratory depression may include close observation, supportive measures, and use of opioid antagonists, depending on the patient’s clinical status [see Overdosage (10)]. Carbon dioxide (CO2) retention from opioid-induced respiratory depression can exacerbate the sedating effects of opioids.

While serious, life-threatening, or fatal respiratory depression can occur at any time during the use of ZOHYDRO ER, the risk is greatest during the initiation of therapy or following a dose increase. Closely monitor patients for respiratory depression when initiating therapy with ZOHYDRO ER and following dose increases.

To reduce the risk of respiratory depression, proper dosing and titration of ZOHYDRO ER are essential [see Dosage and Administration (2)]. Overestimating the ZOHYDRO ER dose when converting patients from another opioid product can result in fatal overdose with the first dose.

Accidental ingestion of even one dose of ZOHYDRO ER, especially by children, can result in respiratory depression and death due to an overdose of hydrocodone.

5.3 Neonatal Opioid Withdrawal Syndrome

Prolonged use of ZOHYDRO ER during pregnancy can result in withdrawal signs in the neonate. Neonatal opioid withdrawal syndrome, unlike opioid withdrawal syndrome in adults, may be life-threatening if not recognized and treated, and requires management according to protocols developed by neonatology experts. If opioid use is required for a prolonged period in a pregnant woman, advise the patient of the risk of neonatal opioid withdrawal syndrome and ensure that appropriate treatment will be available. Neonatal opioid withdrawal syndrome presents as irritability, hyperactivity and abnormal sleep pattern, high pitched cry, tremor, vomiting, diarrhea and failure to gain weight. The onset, duration, and severity of neonatal opioid withdrawal syndrome vary based on the specific opioid used, duration of use, timing and amount of last maternal use, and rate of elimination of the drug by the newborn.

5.4 Interactions with Central Nervous System Depressants

Patients must not consume alcoholic beverages, or prescription or non-prescription products containing alcohol, while on ZOHYDRO ER therapy. The co-ingestion of alcohol with ZOHYDRO ER may result in increased plasma levels and a potentially fatal overdose of hydrocodone [see Clinical Pharmacology (12.3)].

Hypotension, profound sedation, coma, respiratory depression, and death may result if ZOHYDRO ER is used concomitantly with alcohol or other central nervous system (CNS) depressants (e.g., sedatives, anxiolytics, hypnotics, neuroleptics, other opioids).

When considering the use of ZOHYDRO ER in a patient taking a CNS depressant, assess the duration of use of the CNS depressant and the patient’s response, including the degree of tolerance that has developed to CNS depression. Additionally, evaluate the patient’s use of alcohol or illicit drugs that cause CNS depression. If the decision to begin ZOHYDRO ER is made, start with a lower ZOHYDRO ER dose than usual (i.e., 20%-30% less), monitor patients for signs of sedation and respiratory depression, and consider using a lower dose of the concomitant CNS depressant [see Drug Interactions (7.2)].

5.5 Use in Elderly, Cachectic, and Debilitated Patients

Life-threatening respiratory depression is more likely to occur in elderly, cachectic, or debilitated patients as they may have altered pharmacokinetics or altered clearance compared to younger, healthier patients. Monitor such patients closely, particularly when initiating and titrating ZOHYDRO ER and when ZOHYDRO ER is given concomitantly with other drugs that depress respiration [see Warnings and Precautions (5.2)].

5.6 Use in Patients with Chronic Pulmonary Disease

Monitor for respiratory depression in patients with significant chronic obstructive pulmonary disease or cor pulmonale, and patients having a substantially decreased respiratory reserve, hypoxia, hypercapnia, or preexisting respiratory depression, particularly when initiating therapy and titrating with ZOHYDRO ER, as in these patients, even usual therapeutic doses of ZOHYDRO ER may decrease respiratory drive to the point of apnea [see Warnings and Precautions (5.2)]. Consider the use of alternative non-opioid analgesics in these patients if possible.

5.7 Hypotensive Effect

ZOHYDRO ER may cause severe hypotension including orthostatic hypotension and syncope in ambulatory patients. There is an added risk to individuals whose ability to maintain blood pressure has been compromised by a depleted blood volume, or after concurrent administration with drugs such as phenothiazines or other agents which compromise vasomotor tone. Monitor these patients for signs of hypotension after initiating or titrating the dose of ZOHYDRO ER. In patients with circulatory shock, ZOHYDRO ER may cause vasodilation that can further reduce cardiac output and blood pressure. Avoid the use of ZOHYDRO ER in patients with circulatory shock.

5.8 Use in Patients with Head Injury and Increased Intracranial Pressure

Monitor patients taking ZOHYDRO ER who may be susceptible to the intracranial effects of CO2 retention (e.g., those with evidence of increased intracranial pressure or brain tumors) for signs of sedation and respiratory depression, particularly when initiating therapy with ZOHYDRO ER. ZOHYDRO ER may reduce respiratory drive, and the resultant CO2 retention can further increase intracranial pressure. Opioids may also obscure the clinical course in a patient with a head injury.

Avoid the use of ZOHYDRO ER in patients with impaired consciousness or coma.

5.9 Use in Patients with Gastrointestinal Conditions

ZOHYDRO ER is contraindicated in patients with known or suspected paralytic ileus. Opioids diminish propulsive peristaltic waves in the gastrointestinal tract and decrease bowel motility. Monitor for decreased bowel motility in post-operative patients receiving opioids. The administration of ZOHYDRO ER may obscure the diagnosis or clinical course in patients with acute abdominal conditions. Hydrocodone may cause spasm of the sphincter of Oddi. Monitor patients with biliary tract disease, including acute pancreatitis.

5.10 Use in Patients with Convulsive or Seizure Disorders

The hydrocodone in ZOHYDRO ER may aggravate convulsions in patients with convulsive disorders, and may induce or aggravate seizures in some clinical settings. Monitor patients with a history of seizure disorders for worsened seizure control during ZOHYDRO ER therapy.

5.11 Avoidance of Withdrawal

Avoid the use of mixed agonist/antagonist (i.e., pentazocine, nalbuphine, and butorphanol) or partial agonist (buprenorphine) analgesics in patients who have received, or are receiving, a course of therapy with a full opioid agonist analgesic, including ZOHYDRO ER. In these patients, mixed agonist/antagonist and partial agonist analgesics may reduce the analgesic effect and/or may precipitate withdrawal symptoms [see Drug Interactions (7.4)]

5.12 Driving and Operating Machinery

ZOHYDRO ER may impair the mental and physical abilities needed to perform potentially hazardous activities such as driving a car or operating machinery. Warn patients not to drive or operate dangerous machinery unless they are tolerant to the effects of ZOHYDRO ER and know how they will react to the medication.

5.13 Cytochrome P450 CYP3A4 Inhibitors and Inducers

Since the CYP3A4 isoenzyme plays a major role in the metabolism of ZOHYDRO ER, drugs that alter CYP3A4 activity may cause changes in clearance of hydrocodone which could lead to changes in hydrocodone plasma concentrations.

Inhibition of CYP3A4 activity by its inhibitors such as macrolide antibiotics (e.g., erythromycin), azole-antifungal agents, (e.g., ketoconazole), and protease inhibitors (e.g., ritonavir), may increase plasma concentrations of hydrocodone and prolong opioid effects.

CYP3A4 inducers, such as rifampin, carbamazepine, and phenytoin, may induce the metabolism of hydrocodone and, therefore, may cause increased clearance of the drug which could lead to a decrease in hydrocodone plasma concentrations, lack of efficacy or, possibly, development of an abstinence syndrome in a patient who had developed physical dependence to hydrocodone.

If co-administration is necessary, monitor patients closely who are currently taking, or discontinuing, CYP3A4 inhibitors or inducers. Evaluate these patients at frequent intervals and consider dose adjustments until stable drug effects are achieved [see Drug Interactions (7.3) and Clinical Pharmacology (12.3)].

6 ADVERSE REACTIONS

The following serious adverse reactions are discussed elsewhere in the labeling:

- Addiction, Abuse, and Misuse [see Warnings and Precautions (5.1)]
- Life-Threatening Respiratory Depression [see Warnings and Precautions (5.2)]
- Neonatal Opioid Withdrawal Syndrome [see Warnings and Precautions (5.3)]
- Interactions with Other CNS Depressants [see Warnings and Precautions (5.4)]
- Hypotensive Effect [see Warnings and Precautions (5.7)]
- Gastrointestinal Conditions [see Warnings and Precautions (5.9)]
- Seizures [see Warnings and Precautions (5.10)]

6.1 Clinical Trial Experience

Because clinical trials are conducted under widely varying conditions, adverse reaction rates observed in the clinical trials of a drug cannot be directly compared to rates in the clinical trials of another drug and may not reflect the rates observed in clinical practice. The safety of ZOHYDRO ER was evaluated in a total of 1,148 subjects in Phase 3 clinical trials.

Table 3 lists the most frequently occurring adverse reactions occurring at a greater frequency than placebo from the placebo-controlled trial in subjects with moderate-to-severe chronic lower back pain.

Table 3. Treatment-Emergent Adverse Events in ≥2% of Subjects During the Open-Label Titration Period and/or the Double-Blind Treatment Period, by Preferred Term —Number (%) of Treated Subjects (Placebo-Controlled Study in Opioid-Experienced Subjects with Moderate-to-Severe Chronic Lower Back Pain)
 | Open-Label Titration Period | Double-Blind Treatment Period
 | ZOHYDRO ER | ZOHYDRO ER | Placebo
Preferred Term | (N = 510) | (n = 151) | (n = 151)
Constipation | 56 (11%) | 12 (8%) | 0 (0%)
Nausea | 50 (10%) | 11 (7%) | 5 (3%)
Somnolence | 24 (5%) | 1 (1%) | 0 (0%)
Fatigue | 21 (4%) | 1 (1%) | 2 (1%)
Headache | 19 (4%) | 0 (0%) | 2 (1%)
Dizziness | 17 (3%) | 3 (2%) | 1 (1%)
Dry mouth | 16 (3%) | 0 (0%) | 0 (0%)
Vomiting | 14 (3%) | 7 (5%) | 1 (1%)
Pruritus | 13 (3%) | 0 (0%) | 0 (0%)
Abdominal pain | 8 (2%) | 4 (3%) | 0 (0%)
Edema peripheral | 7 (1%) | 4 (3%) | 0 (0%)
Upper respiratory tract infection | 7 (1%) | 5 (3%) | 1 (1%)
Muscle spasms | 6 (1%) | 4 (3%) | 2 (1%)
Urinary tract infection | 4 (1%) | 8 (5%) | 3 (2%)
Back pain | 4 (1%) | 6 (4%) | 5 (3%)
Tremor | 1 (0%) | 4 (3%) | 1 (1%)

The common (≥1% to <10%) adverse drug reactions reported at least once by subjects treated with ZOHYDRO ER in the Phase 3 clinical trials and not represented in Table 3 were:

Gastrointestinal Disorders: abdominal discomfort, abdominal pain, gastroesophageal reflux disease
General Disorders and Administration Site Conditions: non-cardiac chest pain, pain, peripheral edema, pyrexia
Injury, Poisoning and Procedural Complications: contusion, fall, foot fracture, joint injury, joint sprain, muscle strain, skin laceration
Investigations: increased blood cholesterol, increased gamma-glutamyltransferase
Metabolism and Nutrition Disorders: dehydration, hypokalemia
Musculoskeletal and Connective Tissue Disorders: arthralgia, musculoskeletal pain, myalgia, neck pain, osteoarthritis, pain in extremity
Nervous System Disorders: lethargy, migraine, paresthesia
Psychiatric Disorders: anxiety, depression, insomnia
Respiratory, Thoracic, and Mediastinal Disorders: cough, dyspnea
Skin and Subcutaneous Tissue Disorders: hyperhidrosis, night sweats, rash
Vascular Disorders: hot flush

7 DRUG INTERACTIONS

7.1 Alcohol

Concomitant use of alcohol with ZOHYDRO ER can result in an increase of hydrocodone plasma levels and potentially fatal overdose of hydrocodone. Instruct patients not to consume alcoholic beverages or use prescription or non-prescription products containing alcohol while on ZOHYDRO ER therapy [see Clinical Pharmacology (12.3)].

7.2 CNS Depressants

The concomitant use of ZOHYDRO ER with other CNS depressants including sedatives, hypnotics, tranquilizers, general anesthetics, phenothiazines, other opioids, and alcohol, can increase the risk of respiratory depression, profound sedation, coma, or death. Monitor patients receiving CNS depressants and ZOHYDRO ER for signs of respiratory depression, sedation, and hypotension.

When combined therapy with any of the above medications is considered, the dose of one or both agents should be reduced [see Dosage and Administration (2.1) and Warnings and Precautions (5.4)].

7.3 Drugs Affecting Cytochrome P450 Isoenzymes

Inhibitors of CYP3A4 and 2D6
Because the CYP3A4 isoenzyme plays a major role in the metabolism of hydrocodone, drugs that inhibit CYP3A4 activity may cause decreased clearance of hydrocodone which could lead to an increase in hydrocodone plasma concentrations and result in increased or prolonged opioid effects. These effects could be more pronounced with concomitant use of CYP2D6 and 3A4 inhibitors. If co-administration with ZOHYDRO ER is necessary, monitor patients for respiratory depression and sedation at frequent intervals and consider dose adjustments until stable drug effects are achieved [see Clinical Pharmacology (12.3)].

Inducers of CYP3A4
Cytochrome P450 3A4 inducers may induce the metabolism of hydrocodone and, therefore, may cause increased clearance of the drug which could lead to a decrease in hydrocodone plasma concentrations, lack of efficacy or, possibly, development of a withdrawal syndrome in a patient who had developed physical dependence to hydrocodone. If co-administration with ZOHYDRO ER is necessary, monitor for signs of opioid withdrawal and consider dose adjustments until stable drug effects are achieved [see Clinical Pharmacology (12.3)].

After stopping the treatment of a CYP3A4 inducer, as the effects of the inducer decline, the hydrocodone plasma concentration will increase which could increase or prolong both the therapeutic and adverse effects, and may cause serious respiratory depression [see Clinical Pharmacology (12.3)].

7.4 Interactions with Mixed Agonist/Antagonist Opioid Analgesics

Mixed agonist/antagonist (i.e., pentazocine, nalbuphine, butorphanol) and partial agonist (buprenorphine) analgesics may reduce the analgesic effect of hydrocodone or precipitate withdrawal symptoms. Avoid the use of mixed agonist/antagonist and partial agonist analgesics in patients receiving ZOHYDRO ER.

7.5 Monoamine Oxidase Inhibitors

The effects of opioid analgesics may be potentiated by monoamine oxidase (MAO) inhibitors. ZOHYDRO ER is not recommended for use in patients who have received MAO inhibitors within 14 days as severe and unpredictable potentiation by MAO inhibitors has been reported with opioid analgesics. No specific interaction between hydrocodone and MAO inhibitors has been observed, but caution in the use of any opioid in patients taking this class of drugs is appropriate.

7.6 Anticholinergics

Anticholinergics or other drugs with anticholinergic activity when used concurrently with opioid analgesics may increase the risk of urinary retention or severe constipation, which may lead to paralytic ileus. Monitor patients for signs of urinary retention and constipation in addition to respiratory and central nervous system depression when ZOHYDRO ER is used concurrently with anticholinergic drugs.

8 USE IN SPECIFIC POPULATIONS

8.1 Pregnancy

Risk Summary
Prolonged use of opioid analgesics during pregnancy may cause neonatal opioid withdrawal syndrome [see Warnings and Precautions (5.3)]. There are no studies of ZOHYDRO ER use in pregnant women. The background risk of major birth defects and miscarriage for the indicated population is unknown. However, the background risk in the U.S. general population of major birth defects is 2-4% and of miscarriage is 15-20% of clinically recognized pregnancies. Rats administered oral hydrocodone during gestation and lactation showed increases in stillborn pups and decreases in pup survival at doses equivalent to the human dose of 100 mg/day. Reduced nursing behavior and decreased body weights were observed at 2 times the human dose. Reduced fetal weights were observed in rabbits administered hydrocodone during the period of organogenesis at doses equivalent to 5 times the human dose of 100 mg/day. In this study, increases in the number of umbilical hernias, irregularly shaped bones, and delays in fetal skeletal maturation were observed at doses 15 times the human dose of 100 mg/day. No fetal malformations were observed in animal reproduction studies with oral administration of hydrocodone bitartrate during organogenesis in rats and rabbits at doses approximately 2 and 10 times a human dose of 100 mg/day, respectively [see Data]. Based on animal data, advise pregnant women of the potential risks to a fetus.

Clinical Considerations
Fetal/neonatal adverse reactions
Prolonged use of opioid analgesics during pregnancy for medical or nonmedical purposes can result in physical dependence in the newborn and neonatal opioid withdrawal syndrome shortly after birth. Observe newborns for symptoms of neonatal opioid withdrawal syndrome, such as poor feeding, diarrhea, irritability, tremor, rigidity, and seizures, and manage accordingly [see Warnings and Precautions (5.3)].

Labor or Delivery
Opioids cross the placenta and may produce respiratory depression and psycho-physiologic effects in neonates. An opioid antagonist such as naloxone must be available for reversal of opioid induced respiratory depression in the neonate. ZOHYDRO ER is not recommended for use in women during and immediately prior to labor, when shorter-acting analgesics or other analgesic techniques are more appropriate. Opioid analgesics, including ZOHYDRO ER, can prolong labor through actions which temporarily reduce the strength, duration and frequency of uterine contractions. However, this effect is not consistent and may be offset by an increased rate of cervical dilatation, which tends to shorten labor.

Data
Animal Data
Oral doses of hydrocodone bitartrate up to 25 mg/kg/day in rats and 50 mg/kg/day in rabbits, equivalent to 2 and 10 times an adult human dose of 100 mg/day, respectively on a mg/m^2 basis, did not result in any fetal malformations. Fetuses of rabbits administered oral doses of 75 mg/kg/day hydrocodone bitartrate (15 times an adult human dose of 100 mg/day on a mg/m^2 basis) during the period of organogenesis exhibited an increased number of malformations consisting of umbilical hernia, and irregularly shaped bones (ulna, femur, tibia and/or fibula). Maternal toxicity was evident at this dose (decreased body weight). In addition, oral hydrocodone bitartrate reduced fetal weights at doses greater than or equal to 25 mg/kg/day (equivalent to approximately 5 times an adult human dose of 100 mg/day on a mg/m^2 basis). Delays in fetal skeletal maturation (reduced ossification of hyoid bodies and xiphoid bones) were seen following dosing with 75 mg/kg/day (a dose equivalent to 15 times an adult human dose of 100 mg/day on a mg/m^2 basis).

Hydrocodone bitartrate administered orally to female rats at oral doses of 10 and 25 mg/kg/day during gestation and lactation resulted in pups which were noted as cold to touch and caused a reduction in fetal viability (increases in the number of stillborn pups and/or pups dying postpartum). The doses causing these effects were equivalent to approximately 1 and 2.4 times an adult human dose of 100 mg/day, on a mg/m^2 basis. Nursing was reduced in pups of mothers administered 25 mg/kg/day which correlated with decreased body weight/body weight gain and food consumption in male pups. Minimal maternal toxicity was evident at 25 mg/kg (decreased body weight).

8.2 Lactation

Risk Summary
Hydrocodone is present in human milk. A published lactation study reports variable concentrations of hydrocodone and hydromorphone (an active metabolite) in breast milk with administration of immediate-release hydrocodone to nursing mothers in the early post-partum period. This lactation study did not assess breastfed infants for potential adverse drug reactions. Lactation studies have not been conducted with extended-release hydrocodone, including ZOHYDRO ER, and no information is available on the effects of the drug on the breastfed infant or the effects of the drug on milk production. Because of the potential for serious adverse reactions, including excess sedation and respiratory depression in a breastfed infant, advise patients that breastfeeding is not recommended during treatment with ZOHYDRO ER.

Clinical Considerations
Infants exposed to ZOHYDRO ER through breast milk should be monitored for excess sedation and respiratory depression. Withdrawal symptoms can occur in breastfed infants when maternal administration of an opioid analgesic is stopped, or when breast-feeding is stopped.

8.3 Females and Males of Reproductive Potential

Infertility
No effects on male fertility were observed with hydrocodone at doses equivalent to 10 times the human dose of 100 mg/day, however, decreases in the weight of male reproductive organs were observed in all treated groups at doses equivalent to 2.4 times the human dose of 100 mg/day and above. Reductions in female fertility indices were observed at doses of hydrocodone equivalent to 2 times the human dose of 100 mg/day and above. These changes are attributed to a hydrocodone-mediated decrease in prolactin levels in the rat. Unique to rodents, prolactin is required for normal estrous cycling and the effects on fertility observed in this study are most likely rodent-specific and not believed to be clinically relevant [see Nonclinical Toxicology (13.1)].

8.4 Pediatric Use

The safety and effectiveness of ZOHYDRO ER in pediatric patients below the age of 18 years have not been established.

8.5 Geriatric Use

Clinical studies of ZOHYDRO ER did not include sufficient numbers of subjects aged 65 and over to determine whether they respond differently from younger subjects. Other reported clinical experience has not identified differences in responses between the elderly and younger patients. In general, dose selection for an elderly patient should be cautious, usually starting at the low end of the dosing range, reflecting the greater frequency of decreased hepatic, renal, or cardiac function, and of the concomitant disease or other drug therapy.

Hydrocodone is known to be substantially secreted by the kidney. Thus the risk of toxic reactions may be greater in patients with impaired renal function due to the accumulation of the parent compound and/or metabolites in the plasma. Because elderly patients are more likely to have decreased renal function, care should be taken in dose selection, and it may be useful to monitor renal function.

Hydrocodone may cause confusion and over-sedation in the elderly; elderly patients generally should be started on low doses of hydrocodone bitartrate and observed closely for adverse events such as respiratory depression.

8.6 Hepatic Impairment

Patients with hepatic impairment may have higher plasma concentrations than those with normal function. No adjustment in starting dose with ZOHYDRO ER is required in patients with mild or moderate hepatic impairment; however, in patients with severe hepatic impairment, start with the lowest dose, 10 mg. Monitor these patients closely for adverse events such as respiratory depression [see Clinical Pharmacology (12.3)].

8.7 Renal Impairment

Patients with renal impairment have higher plasma concentrations than those with normal function. Use a low initial dose of ZOHYDRO ER in patients with renal impairment and monitor closely for adverse events such as respiratory depression [see Clinical Pharmacology (12.3)].

9 DRUG ABUSE AND DEPENDENCE

9.1 Controlled Substance

ZOHYDRO ER contains hydrocodone bitartrate, a Schedule II controlled substance with a high potential for abuse similar to fentanyl, hydromorphone, methadone, morphine, oxycodone, and oxymorphone. The high drug content in the extended-release formulation adds to the risk of adverse outcomes from abuse and misuse.

9.2 Abuse

All patients treated with opioids require careful monitoring for signs of abuse and addiction as use of opioid analgesic products carries the risk of addiction even under appropriate medical use.

Drug abuse is the intentional non-therapeutic use of an over-the-counter or prescription drug, even once, for its rewarding psychological or physiological effects. Drug abuse includes, but is not limited to the following examples: the use of a prescription or over-the-counter drug to get “high,” or the use of steroids for performance enhancement and muscle build up.

Drug addiction is a cluster of behavioral, cognitive, and physiological phenomena that develop after repeated substance use and include: a strong desire to take the drug, difficulties in controlling its use, persisting in its use despite harmful consequences, a higher priority given to drug use than to other activities and obligations, increased tolerance, and sometimes a physical withdrawal.

"Drug-seeking" behavior is very common to addicts and drug abusers. Drug seeking tactics include, but are not limited to, emergency calls or visits near the end of office hours, refusal to undergo appropriate examination, testing or referral, repeated claims of “loss” of prescriptions, tampering with prescriptions and reluctance to provide prior medical records or contact information for other treating physician(s). “Doctor shopping” (visiting multiple prescribers) to obtain additional prescriptions is common among drug abusers, people with untreated addiction, and criminals seeking drugs to sell. Preoccupation with achieving adequate pain relief can be appropriate behavior in a patient with poor pain control.

Abuse and addiction are separate and distinct from physical dependence and tolerance. Physicians should be aware that addiction may not be accompanied by concurrent tolerance and symptoms of physical dependence in all addicts. In addition, abuse of opioids can occur in the absence of true addiction.

ZOHYDRO ER, like other opioids, can be diverted for non-medical use into illicit channels of distribution. Careful record-keeping of prescribing information, including quantity, frequency, and renewal requests, as required by law, is strongly advised.

Proper assessment of the patient, proper prescribing practices, periodic re-evaluation of therapy, and proper dispensing, storage, and disposal are appropriate measures that help to limit abuse of opioid drugs.

Risks Specific to Abuse of ZOHYDRO ER

ZOHYDRO ER is for oral use only. Abuse of ZOHYDRO ER poses a risk of overdose and death. The risk is increased with concurrent use of ZOHYDRO ER with alcohol and other central nervous system depressants. Taking cut, broken, chewed, crushed, or dissolved ZOHYDRO ER enhances drug release and increases the risk of overdose and death.

With intravenous abuse, the inactive ingredients in ZOHYDRO ER can result in death, local tissue necrosis, infection, pulmonary granulomas, and increased risk of endocarditis and valvular heart injury. Parenteral drug abuse is commonly associated with transmission of infectious diseases such as hepatitis and HIV.

9.3 Dependence

Both tolerance and physical dependence can develop during chronic opioid therapy. Tolerance is the need for increasing doses of opioids to maintain a defined effect such as analgesia (in the absence of disease progression or other external factors). Tolerance may occur to both the desired and undesired effects of drugs, and may develop at different rates for different effects.

Physical dependence results in withdrawal symptoms after abrupt discontinuation or a significant dose reduction of a drug. Withdrawal also may be precipitated through the administration of drugs with opioid antagonist activity, e.g., naloxone, nalmefene, mixed agonist/antagonist analgesics (pentazocine, butorphanol, nalbuphine), or partial agonists (buprenorphine). Physical dependence may not occur to a clinically significant degree until after several days to weeks of continued opioid usage.

ZOHYDRO ER should not be abruptly discontinued [see Dosage and Administration (2.3)]. If ZOHYDRO ER is abruptly discontinued in a physically-dependent patient, an abstinence syndrome may occur. Some or all of the following can characterize this syndrome: restlessness, lacrimation, rhinorrhea, yawning, perspiration, chills, myalgia, and mydriasis. Other signs and symptoms also may develop, including: irritability, anxiety, backache, joint pain, weakness, abdominal cramps, insomnia, nausea, anorexia, vomiting, diarrhea, increased blood pressure, respiratory rate, or heart rate.

Infants born to mothers physically dependent on opioids will also be physically dependent and may exhibit respiratory difficulties and withdrawal symptoms [see Use in Specific Populations (8.1, 8.2, 8.3)].

10 OVERDOSAGE

Clinical Presentation

Acute overdosage with ZOHYDRO ER can be manifested by respiratory depression, somnolence progressing to stupor or coma, skeletal muscle flaccidity, cold and clammy skin, constricted pupils, and, sometimes, pulmonary edema, bradycardia, hypotension, and death. Marked mydriasis rather than miosis may be seen due to severe hypoxia in overdose situations [see Clinical Pharmacology (12.2)].

Treatment of Overdose

In case of overdose, priorities are the re-establishment of a patent and protected airway and institution of assisted or controlled ventilation if needed. Employ other supportive measures (including oxygen and vasopressors) in the management of circulatory shock and pulmonary edema accompanying overdose as indicated. Cardiac arrest or arrhythmias will require advanced life support techniques.

The opioid antagonists, naloxone or nalmefene, are specific antidotes to respiratory depression resulting from opioid overdose. Opioid antagonists should not be administered in the absence of clinically significant respiratory or circulatory depression secondary to hydrocodone overdose. Such agents should be administered cautiously to persons who are known, or suspected to be, physically dependent on ZOHYDRO ER. In such cases, an abrupt or complete reversal of opioid effects may precipitate an acute withdrawal syndrome.

Because the duration of reversal would be expected to be less than the duration of action of ZOHYDRO ER, carefully monitor the patient until spontaneous respiration is reliably reestablished. ZOHYDRO ER will continue to release hydrocodone and add to the hydrocodone load for 24 to 48 hours or longer following ingestion necessitating prolonged monitoring. If the response to opioid antagonists is suboptimal or not sustained, additional antagonist should be administered as directed in the product’s prescribing information.

In an individual physically dependent on opioids, administration of the usual dose of the antagonist will precipitate an acute withdrawal syndrome. The severity of the withdrawal syndrome produced will depend on the degree of physical dependence and the dose of the antagonist administered. If a decision is made to treat serious respiratory depression in the physically dependent patient, administration of the antagonist should begin with care and by titration with smaller than usual doses of the antagonist.

11 DESCRIPTION

ZOHYDRO ER (hydrocodone bitartrate) extended-release capsules are hard gelatin capsules for oral administration. Hydrocodone bitartrate is an opioid agonist and occurs as fine, white crystals, or as a crystalline powder.

The chemical name is 4,5(alpha)-epoxy-3-methoxy-17-methylmorphinan-6-one tartrate (1:1) hydrate (2:5) or morphinan-6-one, 4,5-epoxy-3-methoxy-17-methyl-, (5 alpha)‑, [R (R*, R*)]-2,3-dihydroxybutanedioate (1:1), hydrate (2:5). It has the following structural formula:

Each ZOHYDRO ER capsule contains either 10, 15, 20, 30, 40, or 50 mg of hydrocodone bitartrate USP and the following inactive ingredients: sugar spheres NF, hypromellose USP, ammonio methacrylate copolymer NF, silicon dioxide NF, talc USP, polyethylene oxide NF, and povidone USP. The capsule shells collectively contain titanium dioxide, FD&C Blue #1, FD&C Red #40, FDA Yellow iron oxide, FD&C Red #3, FDA Black iron oxide, FDA Red iron oxide, and gelatin.

12 CLINICAL PHARMACOLOGY

12.1 Mechanism of Action

Hydrocodone is a semi-synthetic opioid agonist with relative selectivity for the mu-opioid (µ) receptor, although it can interact with other opioid receptors at higher doses. Hydrocodone acts as a full agonist, binding to and activating opioid receptors at sites in the peri-aquaductal and peri-ventricular gray matter, the ventro-medial medulla and the spinal cord to produce analgesia. The analgesia, as well as the euphoriant, respiratory depressant and physiologic dependence properties of μ agonist opioids like hydrocodone, result principally from agonist action at the μ receptors.

12.2 Pharmacodynamics

Effects on the Central Nervous System
The principal therapeutic action of hydrocodone is analgesia. In common with other opioids, hydrocodone causes respiratory depression, in part by a direct effect on the brainstem respiratory centers. The respiratory depression involves a reduction in the responsiveness of the brainstem respiratory centers to both increases in carbon dioxide tension and electrical stimulation. Opioids depress the cough reflex by direct effect on the cough center in the medulla.

Hydrocodone causes miosis, even in total darkness. Pinpoint pupils are a sign of opioid overdose but are not pathognomonic (e.g., pontine lesions of hemorrhagic or ischemic origin may produce similar findings). Marked mydriasis rather than miosis may be seen with hypoxia in overdose situations [see Overdosage (10)]. In addition to analgesia, the widely diverse effects of hydrocodone include drowsiness, changes in mood, decreased gastrointestinal motility, nausea, vomiting, and alterations of the endocrine and autonomic nervous system [see Clinical Pharmacology (12.1)].

Effects on the Gastrointestinal Tract and Other Smooth Muscle
Hydrocodone causes a reduction in motility associated with an increase in smooth muscle tone in the antrum of the stomach and duodenum. Digestion of food in the small intestine is delayed and propulsive contractions are decreased. Propulsive peristaltic waves in the colon are decreased, while tone may be increased to the point of spasm resulting in constipation. Other opioid-induced effects may include a reduction in gastric, biliary and pancreatic secretions, spasm of sphincter of Oddi, and transient elevations in serum amylase.

Effects on the Cardiovascular System
Hydrocodone may produce release of histamine with or without associated peripheral vasodilation. Manifestations of histamine release and/or peripheral vasodilation may include pruritus, flushing, red eyes, sweating, and/or orthostatic hypotension.

Effects on the Endocrine System
Opioids may influence the hypothalamic-pituitary-adrenal or -gonadal axes. Some changes that can be seen include an increase in serum prolactin, and decreases in plasma cortisol and testosterone. Clinical signs and symptoms may manifest from these hormonal changes.

Effects on the Immune System
In vitro and animal studies indicate that opioids have a variety of effects on immune functions, depending on the context in which they are used. The clinical significance of these findings is unknown.

Concentration—Efficacy Relationships
The minimum effective plasma concentration of hydrocodone for analgesia varies widely among patients, especially among patients who have been previously treated with agonist opioids. As a result, individually titrate patients to achieve a balance between therapeutic and adverse effects. The minimum effective analgesic concentration of hydrocodone for any individual patient may increase over time due to an increase in pain, progression of disease, development of a new pain syndrome and/or potential development of analgesic tolerance.

Concentration—Adverse Experience Relationships
There is a general relationship between increasing opioid plasma concentration and increasing frequency of adverse experiences such as nausea, vomiting, CNS effects, and respiratory depression.

The dose of ZOHYDRO ER must be individualized [see Dosage and Administration (2.1)]. The effective analgesic dose for some patients will be too high to be tolerated by other patients.

12.3 Pharmacokinetics

As compared to immediate-release hydrocodone combination products, ZOHYDRO ER at similar daily doses results in similar overall exposure but with lower maximum concentrations. The half-life is also longer due to the prolonged duration of absorption. Based on the half-life of hydrocodone, steady-state should be obtained after 3 days of dosing. Following 7 days of dosing, AUC and Cmax increase approximately two-fold as compared to the first day of dosing. The pharmacokinetics of ZOHYDRO ER have been shown to be independent of dose up to a dose of 50 mg.

Absorption
ZOHYDRO ER capsules exhibit peak plasma concentrations occurring approximately 5 hours after dose administration.

Food Effects
Food has no significant effect on the extent of absorption of hydrocodone from ZOHYDRO ER. Although there was no evidence of dose dumping associated with this formulation under fasted and fed conditions, peak plasma concentration of hydrocodone increased by 27% when a ZOHYDRO ER 20 mg capsule was administered with a high-fat meal.

Distribution
Although the extent of protein binding of hydrocodone in human plasma has not been definitively determined, structural similarities to related opioid analgesics suggest that hydrocodone is not extensively protein bound. As most agents in the 5-ring morphinan group of semi-synthetic opioids bind plasma protein to a similar degree (range 19% [hydromorphone] to 45% [oxycodone]), hydrocodone is expected to fall within this range.

Metabolism
Hydrocodone exhibits a complex pattern of metabolism, including N-demethylation, O-demethylation, and 6-keto reduction to the corresponding 6-α-and 6-β-hydroxy metabolites. CYP3A4 mediated N-demethylation to norhydrocodone is the primary metabolic pathway of hydrocodone with a lower contribution from CYP2D6 mediated O-demethylation to hydromorphone. Hydromorphone is formed from the O-demethylation of hydrocodone and may contribute to the total analgesic effect of hydrocodone. Therefore, the formation of these and related metabolites can, in theory, be affected by other drugs [see Drug Interactions (7.3)]. Published in vitro studies have shown that N-demethylation of hydrocodone to form norhydrocodone can be attributed to CYP3A4 while O-demethylation of hydrocodone to hydromorphone is predominantly catalyzed by CYP2D6 and to a lesser extent by an unknown low affinity CYP enzyme.

Excretion
Hydrocodone and its metabolites are eliminated primarily in the kidneys, with a mean apparent plasma half-life after ZOHYDRO ER administration of approximately 8 hours.

Interactions with Alcohol
The rate of absorption of ZOHYDRO ER 50 mg was affected by co-administration with 40% alcohol in the fasted state, as exhibited by an increase in peak hydrocodone concentrations (on average 2.4-fold increase with maximum increase of 3.9-fold in one subject) and a decrease in the time to peak concentrations. The extent of absorption was increased on average 1.2-fold with maximum increase of 1.7-fold in one subject with 40% alcohol [see Warnings and Precautions (5.4)].

Special Populations
Elderly (≥ 65 years)
No significant pharmacokinetic differences by age were observed based on population pharmacokinetic analysis.

Gender
No significant pharmacokinetic differences by gender were observed based on population pharmacokinetic analysis.

Hepatic Impairment
After a single dose of 20 mg ZOHYDRO ER in 20 patients with mild to moderate hepatic impairment based on Child-Pugh classifications, mean hydrocodone Cmax values were 25 ± 5, 24 ± 5, and 22 ± 3.3 ng/mL for moderate and mild impairment, and normal subjects, respectively. Mean hydrocodone AUC values were 509 ± 157, 440 ± 124, and 391 ± 74 ng•h/mL for moderate and mild impairment, and normal subjects, respectively. Hydrocodone Cmax values were 8-10% higher in patients with hepatic impairment while AUC values were 10% and 26% higher in patients with mild and moderate hepatic impairment, respectively. Severely impaired subjects were not studied [see Use in Specific Populations (8.6)].

Renal Impairment
After a single dose of 20 mg ZOHYDRO ER in 28 patients with mild, moderate, or severe renal impairment based on Cockcroft-Gault criteria, mean hydrocodone Cmax values were 26 ± 6.0, 28 ± 7.5, 21 ± 5.1 and 19 ± 4.4 ng/mL for severe, moderate, mild renal impairment, and normal subjects, respectively. Mean hydrocodone AUC values were 487 ± 123, 547 ± 184, 391 ± 122 and 343 ± 105 ng•h/mL for severe, moderate, mild renal impairment, and normal subjects, respectively. Hydrocodone Cmax values were 15%, 48%, and 41% higher and AUC values were 15%, 57% and 44% higher in patients with mild, moderate, and severe renal impairment, respectively [see Use in Specific Populations (8.7)].

Drug-Drug Interactions
While comprehensive PK drug-drug interaction studies (other than alcohol) have not been performed in humans receiving hydrocodone, published in vitro and human PK studies indicate that conversion of hydrocodone to its primary metabolite, norhydrocodone and lesser metabolite, hydromorphone, is mediated by the cytochrome P450 enzyme system. N-demethylation of hydrocodone to form norhydrocodone is attributed to CYP3A4 and O-demethylation of hydrocodone to hydromorphone is predominantly catalyzed by CYP2D6 and to a lesser extent by an unknown low affinity CYP enzyme.

CYP3A4 Inhibitors and Inducers
An increase in CYP3A4 activity by initiation of CYP3A4 inhibiting drugs or discontinuation of CYP3A4 inducing drugs could alter the metabolic profile of hydrocodone causing a slowing of hydrocodone clearance, and lead to elevated hydrocodone concentrations and effects, which could be more pronounced with concomitant use of cytochrome P450 CYP3A4 inhibitors. Initiation of a CYP3A4 inducing drug can lower hydrocodone plasma levels and may induce an opioid-withdrawal syndrome [see Warnings and Precautions (5.13) and Drug Interactions (7.3)].

13 NONCLINICAL TOXICOLOGY

13.1 Carcinogenesis, Mutagenesis, Impairment of Fertility

Carcinogenesis
Long-term animal studies to evaluate the carcinogenic potential of hydrocodone have not been conducted.

Mutagenesis
Hydrocodone bitartrate was genotoxic in an in vitro chromosomal aberration assay in the presence of metabolic activation. No evidence of clastogenicity was observed in this assay in the absence of metabolic activation. No evidence of DNA damage was found in an in vivo comet assay in mouse liver. There was no evidence of genotoxic potential in an in vitro bacterial reverse mutation assay (Salmonella typhimurium and Escherichia coli) or in an assay for chromosomal aberrations (in vivo mouse bone marrow micronucleus assay).

Impairment of Fertility
In a fertility study, rats were administered once daily by oral gavage the vehicle or hydrocodone bitartrate at doses of 25, 75, and 100 mg/kg/day (equivalent to approximately 2, 7, and 10 times an adult human dose of 100 mg/day, on a mg/m^2 basis). Male and female rats were dosed before cohabitation (up to 28 days), during the cohabitation and until gestation day 7 (females) or necropsy (males; 2-3 weeks post-cohabitation). Hydrocodone bitartrate did not affect reproductive function in males, although the weights of male reproductive organs were decreased at all doses. Doses of 25 mg/kg/day and greater in females reduced the rate at which females became pregnant which correlated with suppression of estrous cyclicity, thought to be due to increases in prolactin. In hydrocodone bitartrate-treated rats that became pregnant, at 25 mg/kg early embryonic development was unaffected (approximately 2 times the adult human daily dose of 100 mg/day on a mg/m^2 basis). In rats, prolactin plays a unique role in the estrous cycle and the clinical relevance of the female rat reproductive findings is uncertain.

14 CLINICAL STUDIES

The efficacy and safety of ZOHYDRO ER have been evaluated in a randomized double-blind, placebo-controlled, multi-center clinical trial in opioid-experienced subjects with moderate to severe chronic low back pain.

14.1 Placebo-Controlled Study in Opioid-Experienced Subjects with Moderate to Severe Chronic Lower Back Pain

A total of 510 subjects currently on chronic opioid therapy entered an open-label conversion and titration phase (up to 6 weeks) with ZOHYDRO ER dosed every 12 hours at an approximated equianalgesic dose of their pre-study opioid medication. For inadequately controlled pain, ZOHYDRO ER was increased by 10 mg per 12-hour dose, once every 3–7 days until a stabilized dose was identified, or a maximum dosage of 100 mg every 12 hours. There were 302 subjects (59%) randomized at a ratio of 1:1 into a 12-week double-blind treatment phase with their fixed stabilized dose of ZOHYDRO ER (40-200 mg daily taken as 20-100 mg, every 12 hours) or a matching placebo. Subjects randomized to placebo were given a blinded taper of ZOHYDRO ER according to a pre-specified tapering schedule. During the treatment phase, subjects were allowed to use rescue medication (hydrocodone 5 mg/500 mg acetaminophen) up to 2 doses (2 tablets) per day. There were 124 treated subjects (82%) that completed the 12-week treatment with ZOHYDRO ER and 59 subjects (39%) with placebo.

ZOHYDRO ER provided greater analgesia compared to placebo. There was a significant difference in the mean changes from Baseline to Week 12 in average weekly pain intensity Numeric Rating Scale (NRS) scores between the two groups.

The percentage of subjects in each group who demonstrated improvement in their NRS pain score at End-of-Study, as compared to Screening is shown in the figure below. The figure is cumulative, so subjects whose change from Screening is, for example, 30% are also included at every level of improvement below 30%. Subjects who did not complete the study were classified as non-responders. Treatment with ZOHYDRO ER produced a greater number of responders, defined as subjects with at least a 30% improvement, as compared to placebo (67.5% vs. 31.1%).

16 HOW SUPPLIED/STORAGE AND HANDLING

ZOHYDRO ER extended-release capsules are supplied in 60-count bottles with a child-resistant closure as follows:

Strength | Capsule Color(s) | Capsule Text | NDC Number
10 mg | White opaque | “ZGNX 10 mg” in black ink | 43376-310-60
15 mg | Light green and white opaque | “ZGNX 15 mg” in black ink | 43376-315-60
20 mg | Light green opaque | “ZGNX 20 mg” in black ink | 43376-320-60
30 mg | Dark blue and white opaque | “ZGNX 30 mg” in black ink | 43376-330-60
40 mg | Dark brown and white opaque | “ZGNX 40 mg” in black ink | 43376-340-60
50 mg | Dark brown opaque | “ZGNX 50 mg” in black ink | 43376-350-60

ZOHYDRO ER contains hydrocodone bitartrate which is a controlled substance and is controlled under Schedule II of the Controlled Substances Act. Hydrocodone, like all opioids, is liable to diversion and misuse and should be handled accordingly. Patients and their families should be instructed to dispose of any ZOHYDRO ER capsules that are no longer needed.

ZOHYDRO ER may be targeted for theft and diversion. Healthcare professionals should contact their State Medical Board, State Board of Pharmacy, or State Control Board for information on how to detect or prevent diversion of this product.

Healthcare professionals should advise patients to store ZOHYDRO ER in a secure place, preferably locked and out of the reach of children and other non-caregivers.

Store at 25°C (77°F); excursions permitted to 15°-30°C (59°-86°F) [see USP Controlled Room Temperature].

Dispense in tight container as defined in the USP, with a child-resistant closure.

Advise patients to dispose of any unused capsules from a prescription as soon as they are no longer needed in accordance with local State guidelines and/or regulations [see Patient Counseling Information (17)].

17 PATIENT COUNSELING INFORMATION

See FDA-approved patient labeling (Medication Guide).

17.1 Information for Patients and Caregivers

Addiction, Abuse, and Misuse
Inform patients that the use of ZOHYDRO ER, even when taken as recommended, can result in addiction, abuse, and misuse, which can lead to overdose or death [see Warnings and Precautions (5.1)]. Instruct patients not to share ZOHYDRO ER with others and to take steps to protect ZOHYDRO ER from theft or misuse.

Life-Threatening Respiratory Depression
Inform patients of the risk of life-threatening respiratory depression, including information that the risk is greatest when starting ZOHYDRO ER or when the dose is increased, and that it can occur even at recommended doses [see Warnings and Precautions (5.2)]. Advise patients how to recognize respiratory depression and to seek medical attention if they are experiencing breathing difficulties.

Accidental Ingestion
Inform patients that accidental ingestion, especially in children, may result in respiratory depression or death [see Warnings and Precautions (5.2)]. Instruct patients to take steps to store ZOHYDRO ER securely and to dispose of unused ZOHYDRO ER by flushing the capsules down the toilet.

Neonatal Opioid Withdrawal Syndrome
Inform female patients of reproductive potential that prolonged use of ZOHYDRO ER during pregnancy can result in neonatal opioid withdrawal syndrome, which may be life-threatening if not recognized and treated [see Warnings and Precautions (5.3)].

Interaction with Alcohol and other CNS Depressants
Instruct patients not to consume alcoholic beverages, as well as prescription and over-the-counter products that contain alcohol, during treatment with ZOHYDRO ER. The co-ingestion of alcohol with ZOHYDRO ER may result in increased plasma levels and a potentially fatal overdose of hydrocodone.

Inform patients that potentially serious additive effects may occur if ZOHYDRO ER is used with alcohol or other CNS depressants and not to use such drugs unless supervised by a healthcare provider.

Important Administration Instructions

Instruct patients how to properly take ZOHYDRO ER, including the following:

- Swallow ZOHYDRO ER capsules whole.
- Do not crush, chew, or dissolve the capsule or its contents.
- Use ZOHYDRO ER exactly as prescribed to reduce the risk of life-threatening adverse reactions (e.g., respiratory depression).
- Do not discontinue ZOHYDRO ER without first discussing the need for a tapering regimen with the prescriber.

Hypotension
Inform patients that ZOHYDRO ER may cause orthostatic hypotension and syncope. Instruct patients how to recognize symptoms of low blood pressure and how to reduce the risk of serious consequences should hypotension occur (e.g., sit or lie down, carefully rise from a sitting or lying position).

Driving or Operating Heavy Machinery
Inform patients that ZOHYDRO ER may impair the ability to perform potentially hazardous activities such as driving a car or operating heavy machinery. Advise patients not to perform such tasks until they know how they will react to the medication.

Constipation
Advise patients of the potential for severe constipation, including management instructions and when to seek medical attention.

Anaphylaxis
Inform patients that anaphylaxis has been reported with ingredients contained in ZOHYDRO ER. Advise patients how to recognize such a reaction and when to seek medical attention.

Pregnancy
Advise female patients that ZOHYDRO ER can cause fetal harm and neonatal opioid withdrawal syndrome and to inform their healthcare provider with a known or suspected pregnancy [see Warnings and Precautions (5.3) and Use in Specific Populations (8.1)].

Lactation
Advise patients that breastfeeding is not recommended during treatment with ZOHYDRO ER [see Use in Specific Populations (8.2)].

Disposal of Unused ZOHYDRO ER
Advise patients to flush the unused capsules down the toilet when ZOHYDRO ER is no longer needed.

ZOHYDRO® ER is a registered trademark of Zogenix®, Inc.

Manufactured for Zogenix®, Inc., San Diego, CA 92130 by Alkermes Gainesville LLC under license from Alkermes Pharma Ireland Limited (APIL), Ireland.

U.S. Patent Nos.: US 6,228,398 and US 6,902,742

Medication Guide
ZOHYDRO® ER (zoh-hye-droh)
(hydrocodone bitartrate) extended-release capsules, CII

ZOHYDRO ER is:

- A strong prescription pain medicine that contains an opioid (narcotic) that is used to treat pain severe enough to require daily, around-the-clock, long-term treatment with an opioid, when other pain treatments such as non-opioid pain medicines or immediate-release opioid medicines do not treat your pain well enough or you cannot tolerate them.
- A long acting (extended-release) opioid pain medicine that can put you at risk for overdose and death. Even if you take your dose correctly as prescribed, you are at risk for opioid addiction, abuse, and misuse that can lead to death.
- Not for use to treat pain that is not around-the-clock.

Important information about ZOHYDRO ER:

- Get emergency help right away if you take too much ZOHYDRO ER (overdose). When you first start taking ZOHYDRO ER, when your dose is changed, or if you take too much (overdose), serious or life-threatening breathing problems that can lead to death may occur.
- Never give anyone else your ZOHYDRO ER. They could die from taking it. Store ZOHYDRO ER away from children and in a safe place to prevent stealing or abuse. Selling or giving away ZOHYDRO ER is against the law.

Do not take ZOHYDRO ER if you have:

- severe asthma, trouble breathing, or other lung problems.
- a bowel blockage or narrowing of the stomach or intestines.

Before taking ZOHYDRO ER, tell your healthcare provider if you have a history of:
• head injury, seizures • liver, kidney, thyroid problems
• problems urinating • pancreas or gallbladder problems
• abuse of street or prescription drugs, alcohol addiction, or mental health problems.
Tell your healthcare provider if you are:

- pregnant or planning to become pregnant. Prolonged use of ZOHYDRO ER during pregnancy can cause withdrawal symptoms in your newborn baby that could be life-threatening if not recognized and treated.
- breastfeeding. Not recommended; may harm your baby.
- taking prescription or over-the-counter medicines, vitamins, or herbal supplements. Taking ZOHYDRO ER with certain other medicines can cause serious side effects that could lead to death.

When taking ZOHYDRO ER:

- Do not change your dose. Take ZOHYDRO ER exactly as prescribed by your healthcare provider.
- Take your prescribed dose every 12 hours, at the same time every day. Do not take more than your prescribed dose in 12 hours. If you miss a dose, take your next dose at your usual time.
- Swallow ZOHYDRO ER whole. Do not cut, break, chew, crush, dissolve, snort, or inject ZOHYDRO ER because this may cause you to overdose and die.

Call your healthcare provider if the dose you are taking does not control your pain.

- Do not stop taking ZOHYDRO ER without talking to your healthcare provider.
- After you stop taking ZOHYDRO ER, flush any unused capsules down the toilet.

While taking ZOHYDRO ER DO NOT:

- Drive or operate heavy machinery, until you know how ZOHYDRO ER affects you. ZOHYDRO ER can make you sleepy, dizzy, or lightheaded.
- Drink alcohol or use prescription or over-the-counter medicines that contain alcohol. Using products containing alcohol during treatment with ZOHYDRO ER may cause you to overdose and die.

The possible side effects of ZOHYDRO ER are:

- constipation, nausea, sleepiness, vomiting, tiredness, headache, dizziness, abdominal pain. Call your healthcare provider if you have any of these symptoms and they are severe.

Get emergency medical help if you have:

- trouble breathing, shortness of breath, fast heartbeat, chest pain, swelling of your face, tongue or throat, extreme drowsiness, light-headedness when you are changing positions, or you are feeling faint.

These are not all the possible side effects of ZOHYDRO ER. Call your doctor for medical advice about side effects. You may report side effects to FDA at 1-800-FDA-1088. For more information go to dailymed.nlm.nih.gov

ZOHYDRO ER is a registered trademark of Zogenix, Inc. Manufactured by: Alkermes Gainesville LLC, Gainesville, GA.. Distributed by: Zogenix, Inc., San Diego, CA 92130, www.ZohydroER.com, 1-866-ZOGENIX (1-866-964-3649).

This Medication Guide has been approved by the U.S. Food and Drug Administration Issue: February 2015

PACKAGE LABEL

Principal Display Panel
NDC 43376-310-60
Zohydro ER
(hydrocodone bitartrate)
Extended-Release Capsules
10 mg
60 Capsules
Rx Only

PACKAGE LABEL

Principal Display Panel
NDC 43376-315-60
Zohydro ER
(hydrocodone bitartrate)
Extended-Release Capsules
15 mg
60 Capsules
Rx Only

PACKAGE LABEL

Principal Display Panel
NDC 43376-320-60
Zohydro ER
(hydrocodone bitartrate)
Extended-Release Capsules
20 mg
60 Capsules
Rx Only

PACKAGE LABEL

Principal Display Panel
NDC 43376-330-60
Zohydro ER
(hydrocodone bitartrate)
Extended-Release Capsules
30 mg
60 Capsules
Rx Only

PACKAGE LABEL

Principal Display Panel
NDC 43376-340-60
Zohydro ER
(hydrocodone bitartrate)
Extended-Release Capsules
40 mg
60 Capsules
Rx Only

PACKAGE LABEL

Principal Display Panel
NDC 43376-350-60
Zohydro ER
(hydrocodone bitartrate)
Extended-Release Capsules
50 mg
60 Capsules
Rx Only